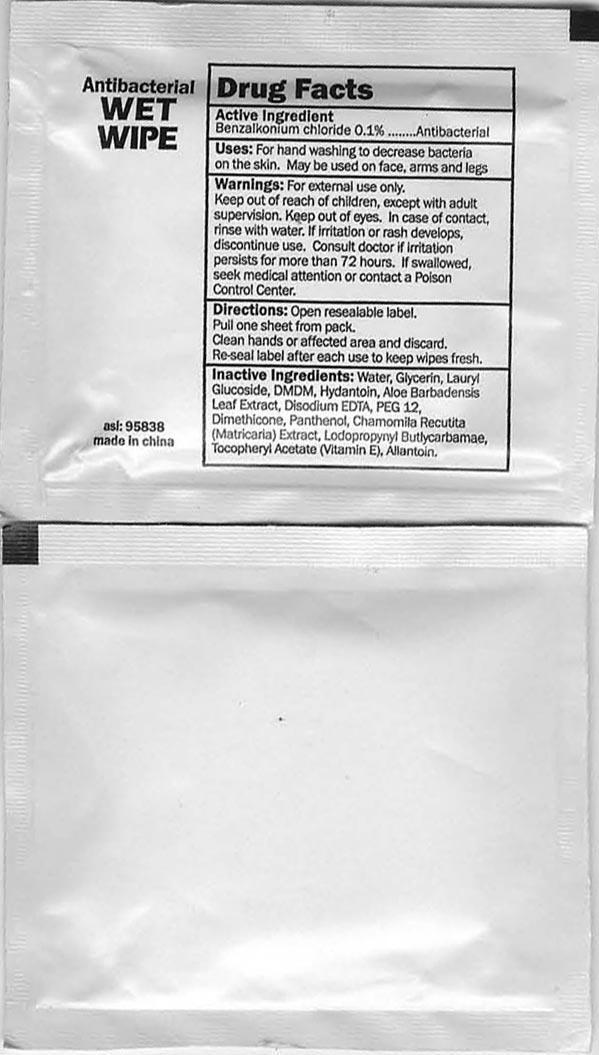 DRUG LABEL: Antibacterial Wet Wipes
NDC: 50672-838 | Form: SWAB
Manufacturer: MC Group Development Ltd.	
Category: otc | Type: HUMAN OTC DRUG LABEL
Date: 20121112

ACTIVE INGREDIENTS: Benzalkonium Chloride 0.1 g/100 g
INACTIVE INGREDIENTS: WATER; Iodopropynyl Butylcarbamate; DMDM Hydantoin; Lauryl Glucoside; GLYCERIN; DEXPANTHENOL; TOCOPHERYL NICOTINATE, D-.ALPHA.; MATRICARIA RECUTITA; PEG-12 DIMETHICONE (300 CST); DISODIUM EDTA-COPPER; ALOE VERA LEAF; Allantoin

Antibacterial Wet Wipes

Active Ingredient

Benzalkonium Chloride

Purpose

Antibacterial

Use

For hand washing to decrease bacteria on the skin.May be used on face,arms and legs.

WARNINGS

For External use only.
Keep out of eyes,Incase of contact,rinse with water.If irritation or rash develops,discontinue use .Consult doctor if irritation persists for more than 72 hours,If swallowed,seek medical attention or contact a Poison Control Center.

keep out of reach of children

Directions

Open resealable label.Pull one sheet from pack.Clean hands or affected area and discard.Re-seal label after each use to keep wipes fresh.

Inactive ingredients

Iodopropynyl Butylcarbamate,DMDM Hydantoin,Lauryl Glucoside,Glycerin,D-Panthenol,Tocopheryl Acetate,Chamomilla Recutita Extract,PEG-12 Dimethicone,Disodium EDTA,Aloe Barbadensis Leaf Extract,Allantoin,Water